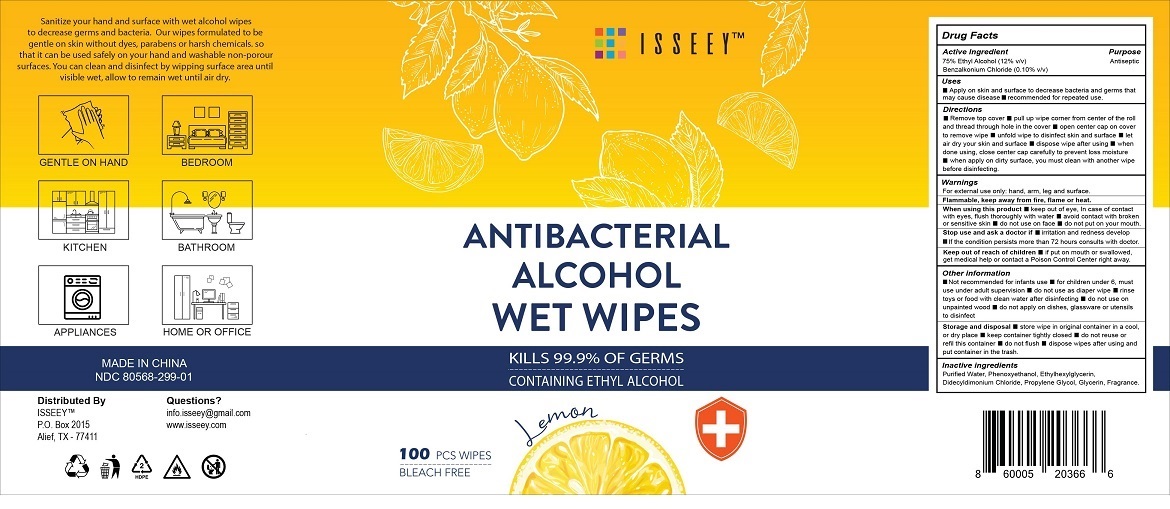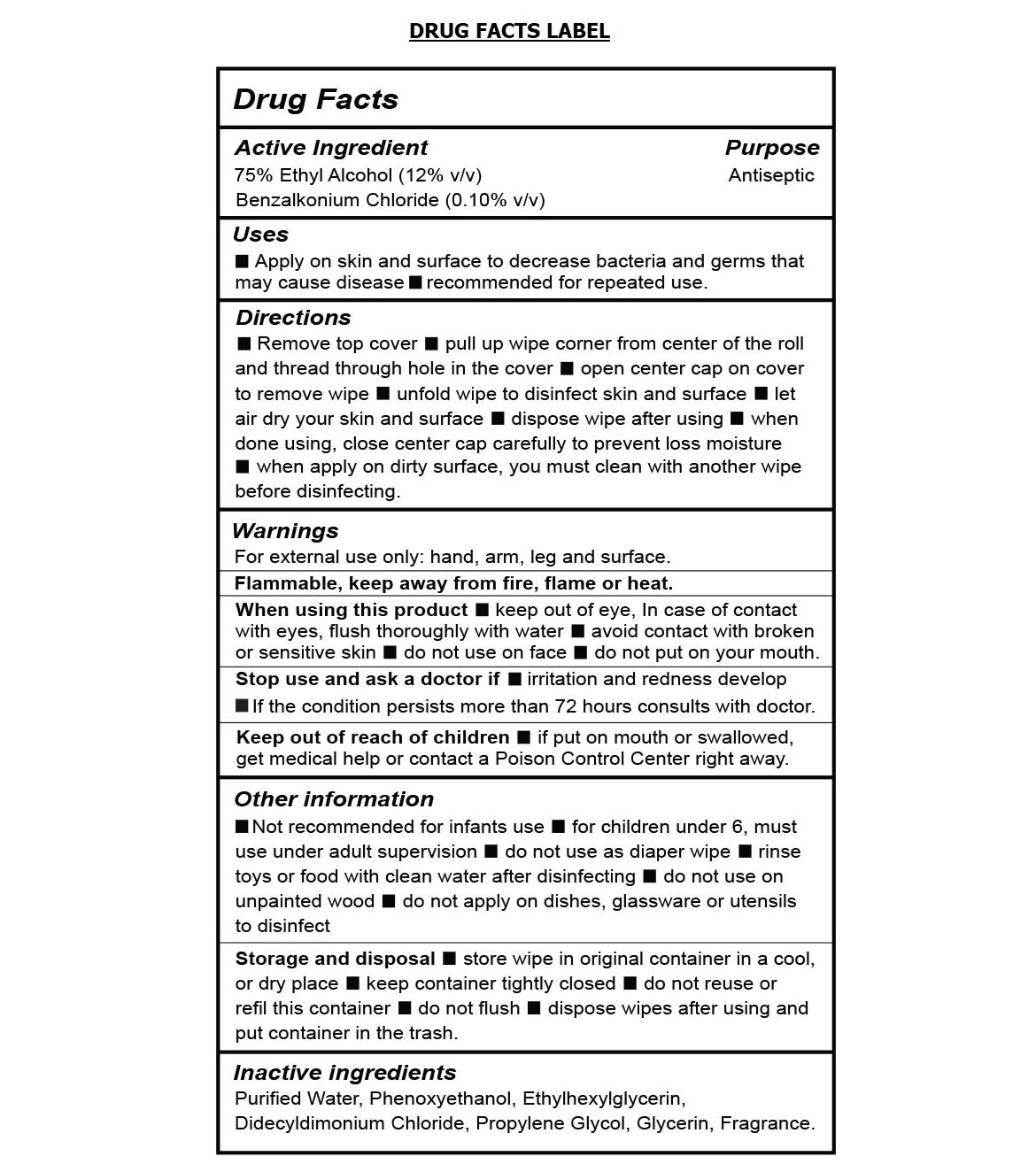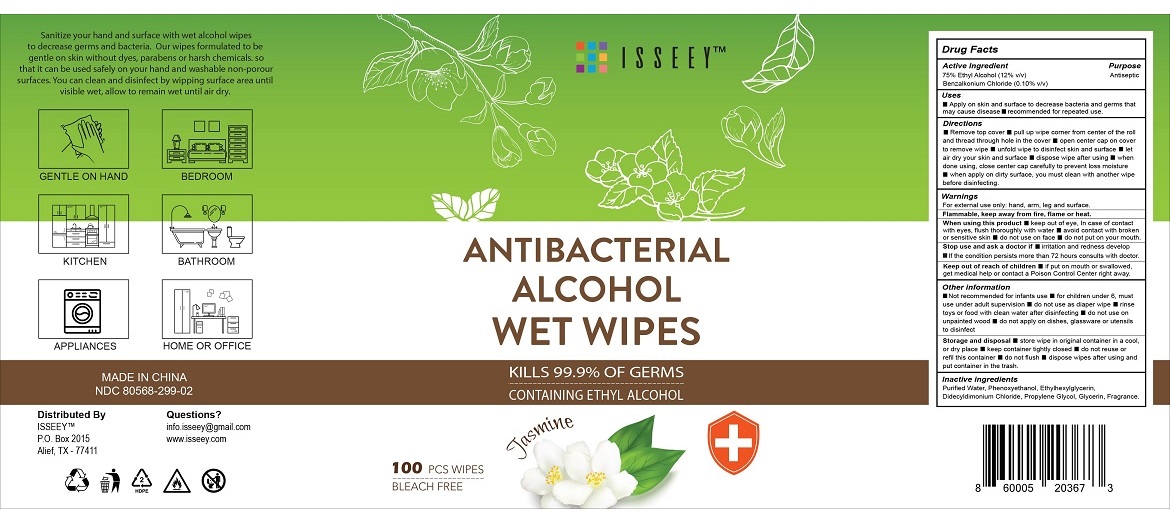 DRUG LABEL: ISSEEY ANTIBACTERIAL ALCOHOL WET WIPES
NDC: 80568-299 | Form: CLOTH
Manufacturer: ISSEEY
Category: otc | Type: HUMAN OTC DRUG LABEL
Date: 20200929

ACTIVE INGREDIENTS: ALCOHOL 75 mL/100 mL; BENZALKONIUM CHLORIDE 0.1 g/100 mL
INACTIVE INGREDIENTS: WATER; PHENOXYETHANOL; ETHYLHEXYLGLYCERIN; DIDECYLDIMONIUM CHLORIDE; PROPYLENE GLYCOL; GLYCERIN

ISSEEY TM - ANTIBACTERIAL ALCOHOL WET WIPES

Active Ingredient

75% Ethyl Alcohol (12% v/v)

Benzalkonium Chloride (0.10% v/v)

Purpose

Antiseptic

Uses

• Apply on skin and surface to decrease bacteria and germs that may cause disease • recommended for repeated use.

Directions

• Remove top cover • pull up wipe corner from center of the roll and thread through hole in the cover • open center cap on cover to remove wipe • unfold wipe to disinfect skin and surface • let air dry your skin and surface • dispose wipe after using • when done using, close center cap carefully to prevent loss moisture • when apply on dirty surface, you must clean with another wipe before disinfecting.

Warnings

For external use only: hand, arm, leg and surface.

Flammable, keep away from fire, flame or heat.

When using this product • keep out of eye, In case of contact with eyes, flush thoroughly with water • avoid contact with broken or sensitive skin • do not use on face • do not put on your mouth.

Stop use ask a doctor if •irritation and redness develop • If the condition persists more than 72 hours consults with doctor.

Keep out of reach of children • if put on mouth or swallowed, get medical help or contact a Poison Control Center right away.

Other information

• Not recommended for infants use • for children under 6, must use under adult supervision • do not use as diaper wipe • rinse toys or food with clean water after disinfecting • do not use on unpainted wood • do not apply on dishes, glassware or utensils to disinfect

Storage and disposal • store wipe in original container in a cool, or dry place • keep container tightly closed • do not reuse or refill this container • do not flush • dispose wipes after using and put container in the trash.

Inactive ingredients

Purified Water, Phenoxyethanol, Ethylhexylglycerin, Didecyldimonium Chloride, Propylene Glycol, Glycerin, Fragrance.

KILLS 99.9% OF GERMS

CONTAINING ETHYL ALCOHOL

BLEACH FREE

Sanitize your hand and surface with wet alcohol wipes to decrease germs and bacteria. Our wipes formulated to be gentle on skin without dyes, parabens or harsh chemicals. so that it can be used safely on your hand and washable non-porous surfaces. You can clean and disinfect by wiping surface area until visible wet, allow to remain wet until air dry.

GENTLE ON HAND

BEDROOM

KITCHEN

BATHROOM

APPLIANCES

HOME OR OFFICE

MADE IN CHINA

Distributed By

ISSEEY TM

P.O. Box 2015

Alief, TX - 77411

Questions?

info.isseey@gmail.com

www.isseey.com